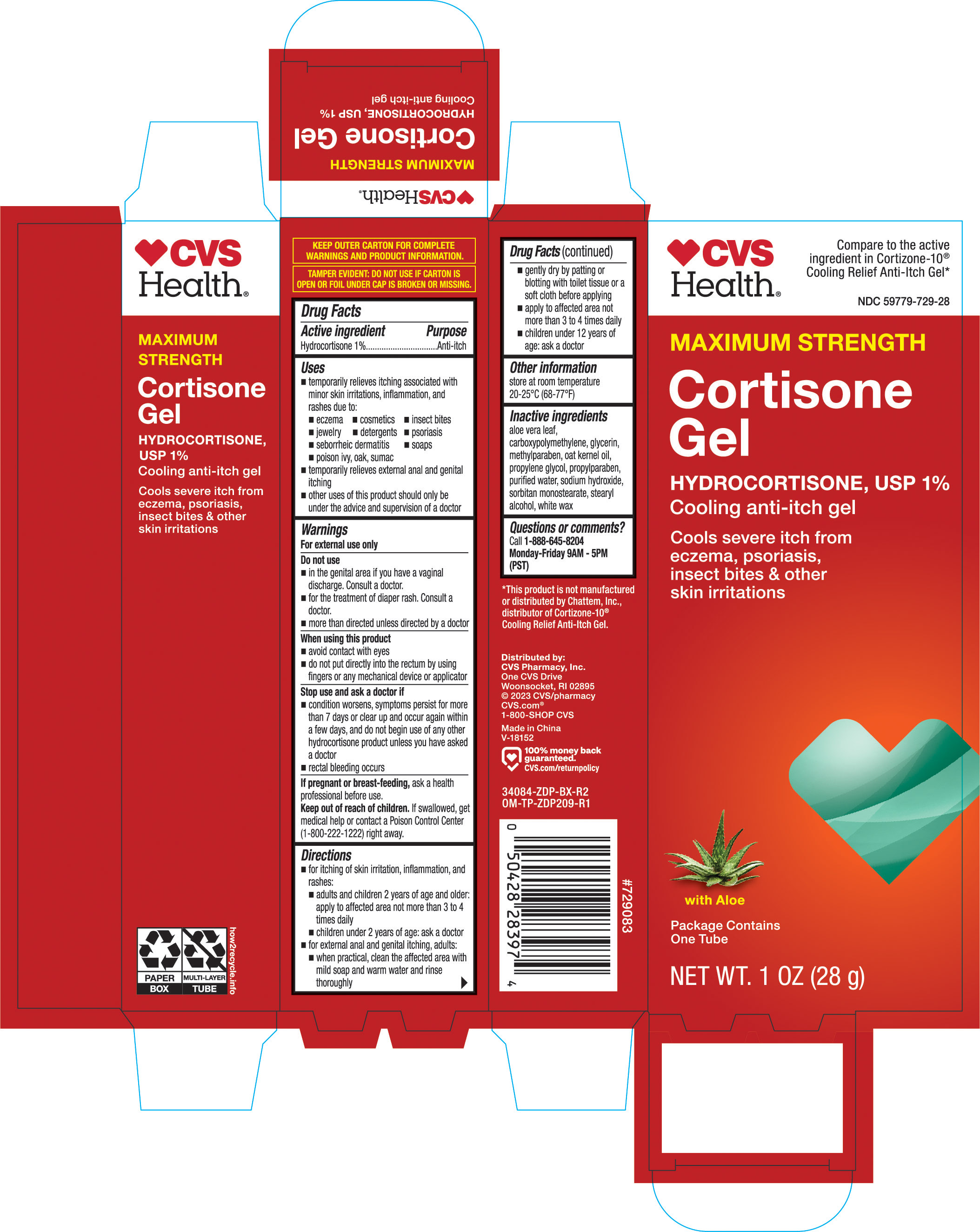 DRUG LABEL: CVS Cools Itch Fast
NDC: 59779-729 | Form: GEL
Manufacturer: CVS Pharmacy, Inc.
Category: otc | Type: HUMAN OTC DRUG LABEL
Date: 20251029

ACTIVE INGREDIENTS: HYDROCORTISONE 1 mg/1 g
INACTIVE INGREDIENTS: ALOE VERA LEAF; CARBOXYPOLYMETHYLENE; GLYCERIN; METHYLPARABEN; OAT KERNEL OIL; PROPYLENE GLYCOL; SODIUM HYDROXIDE; SORBITAN MONOSTEARATE; STEARYL ALCOHOL; WHITE WAX; WATER; PROPYLPARABEN

CVS Cortisone Cooling Gel 1 oz 34084 ZDP

Active ingredients Purpose

Hydrocortisone 1%......................... Anti-itch

PURPOSE

Uses for the temporary relief of itching associated with minor skin irritations, inflammation, and rashes due to:

- eczema
- insect bites
- poison ivy
- posion oak
- poison sumac
- soaps
- jewlery
- detergents
- cosmetics
- psoriasis
- seborrheic dematitis
- temporarily relievs external anal and genital itching
- other uses of this product should be only under the advice and supervision of a doctor

Warnings

For external use only

Do not use

- in the genital area if you have a vaginal discharge. Consult a doctor.
- for the treatment of diaper rash. Consult a doctor.
- more than directed unless directed by a doctor

When using this product

- avoid contact with the eyes
- do not put directly into the rectum by using fingers or any mechanical device or applicator

Stop use and ask a doctor if

- stop use and ask a doctor if
- condition worsens, symptoms persist for more than 7 days or clear up and occur again within a few days, and do not begin use of any other hydrocortisone product unless you have asked a doctor
- rectal bleeding occurs

Keep out of reach of children. If swallowed, get medical help or contact a Poison Control Center right away.

PREGNANCY OR BREAST FEEDING

If pregnant or breast-feeding, ask a health professional before use.

Keep out of reach of children. If swallowed, get medical help or contact a Poison Control Center (1-800-222-1222) right away

Directions

- for itching of skin irritation, inflammation, and rashes:
- adults and children 2 years of age and older: apply to affected area not more than 3 to 4 times daily
- children under 2 years of age: ask a doctor
- for external anal and genital itching, adults:
- when practical, clean the affected area with mild soap and warm water and rinse thoroughly
- gently dry by patting or blotting with toilet tissure or a soft cloth before applying
- apply to affected area not more than 3 to 4 times daily
- children under 12 years of age: consult a doctor

Other information

- store at room temperature 20-25°C (68-77°F)

Inactive ingredients

aloe vera leaf, carboxypolymethylene, glycerin, methylparaben, oat kernel oil, propylene glycol, propylparaben, purified water, sodium hydroxide, sorbitan monostearate, stearyl alcohol, water, white wax

DOSAGE AND ADMINISTRATION

DISTRIBUTED BY:

ONE CVS DRIVE

WOONSOCKET, RI 02895 USA